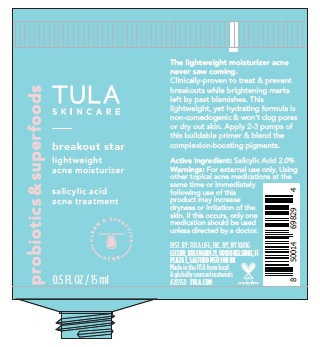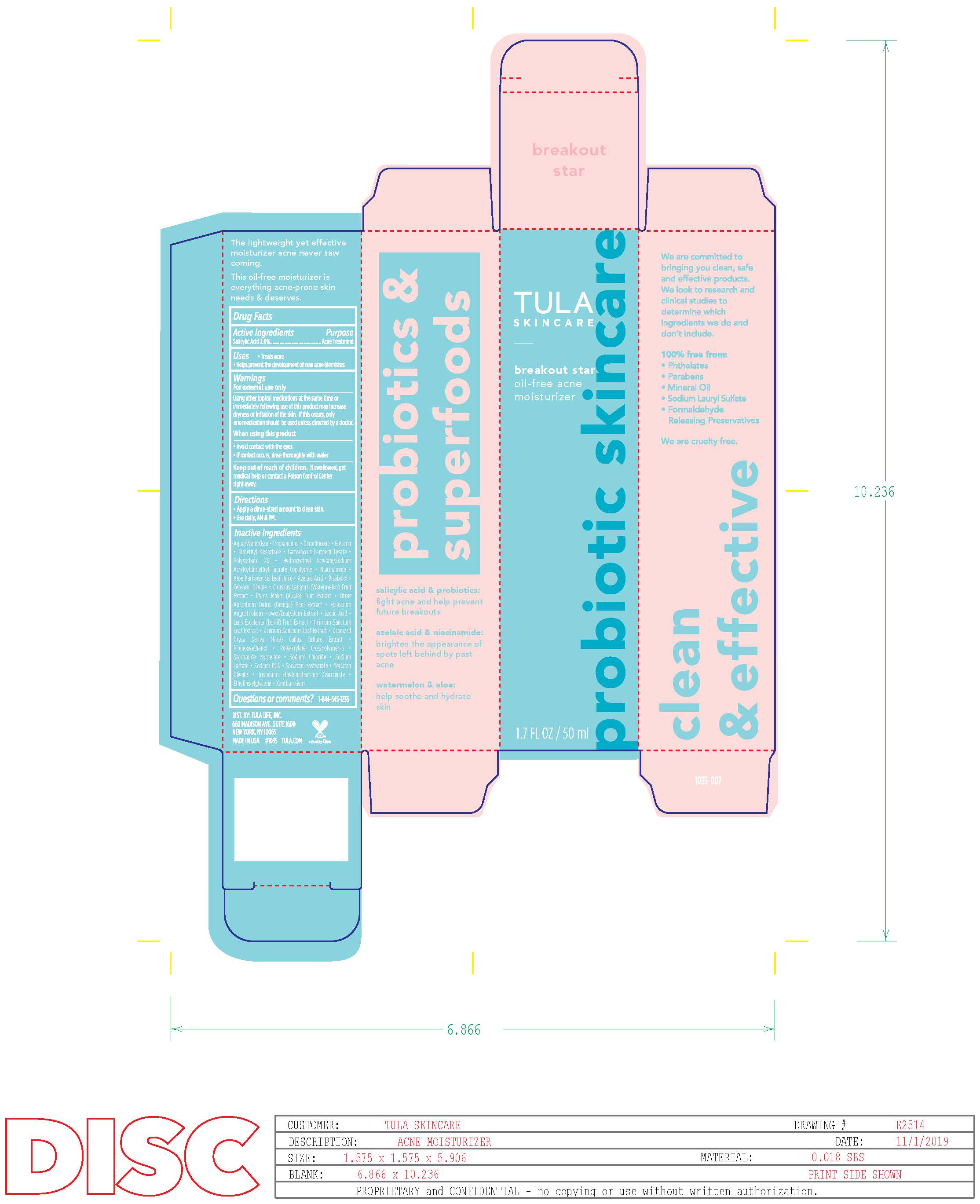 DRUG LABEL: TULA breakout star oil-free acne moisturizer
NDC: 72296-020 | Form: LIQUID
Manufacturer: Tula Life LLC
Category: otc | Type: HUMAN OTC DRUG LABEL
Date: 20240321

ACTIVE INGREDIENTS: SALICYLIC ACID 2 g/100 g
INACTIVE INGREDIENTS: WATER; PROPANEDIOL; DIMETHICONE; GLYCERIN; DIMETHYL ISOSORBIDE; LACTOCOCCUS LACTIS; POLYSORBATE 20; HYDROXYETHYL ACRYLATE/SODIUM ACRYLOYLDIMETHYL TAURATE COPOLYMER (100000 MPA.S AT 1.5%); NIACINAMIDE; ALOE VERA LEAF; AZELAIC ACID; .ALPHA.-BISABOLOL, (+)-; CETEARYL OLIVATE; CITRULLUS LANATUS WHOLE; CITRUS AURANTIUM FLOWER; EPILOBIUM ANGUSTIFOLIUM WHOLE; LACTIC ACID; ORYZA SATIVA WHOLE; PHENOXYETHANOL; SACCHARIDE ISOMERATE; SODIUM CHLORIDE; SODIUM LACTATE; SORBITAN ISOSTEARATE; SORBITAN OLIVATE; TRISODIUM ETHYLENEDIAMINE DISUCCINATE; ETHYLHEXYLGLYCERIN; XANTHAN GUM; APPLE; WATERMELON; LENTIL

DRUG FACTS

Active Ingredients

Salicylic Acid 2.0%

Purpose

Acne Treatment

Uses

• treats acne

• Helps prevent the development or new acne blemishes

Warnings

For external use only
Using other topical medications at the same time or
immediately following use of this product may increase
dryness or irritation of the skin. If this occurs, only one
medication should be used unless directed by a doctor.

When using this product
• avoid contact with the eyes
• if contact occurs, rinse thoroughly with water

Keep out of reach of children. If swallowed, get medical help
or contact a Poison Control Center right away.

Directions

• clean the skin thoroughly before applying this product
• cover the entire affected area with a thin layer one to three
times daily
• because excessive drying of the skin may occur, start with
one application daily, then gradually increase to two or three
times daily if needed or as directed by a doctor
• if bothersome dryness or peeling occurs, reduce application
to once a day or every other day

Inactive ingredients

Aqua/Water/Eau, Propanediol, Dimethicone, Glycerin, Dimethyl Isosorbide, Lactococcus Ferment Lysate, Polysorbate 20, Hydroxyethyl Acrylate/Sodium Acryloyldimethyl Taurate Copolymer, Niacinamide, Aloe Barbadensis Leaf Juice, Azelaic Acid, Bisabolol, Cetearyl Olivate, Cirusllus Lanatus (Watermelon) Fruit Extract, Pyrus Malus (Apple) Fruit Extract, Citrus Aurantium Dulcis (Orange) Peel Extract, Epilobium
Angustifolium Flower/Leaf/Stem Extract, Lactic Acid, Lens Esculenta (Lentil) Fruit Extract, Ocimum Sanctum Leaf Extract, Ozonized Oryza Sativa (Rice) Callus Culture Extract, Phenoxyethanol, Polyacrylate Crosspolymer-6, Saccharide Isomerate, Sodium Chloride, Sodium Lactate, Sodium PCA, Sorbitan Isostearate, Sorbitan Olivate, Trisodium Ethylenediamine Disuccinate, Ethylhexylglycerin, Xanthan Gum

Questions or Comments?

1-844-545-1236

Principal Display Panel

72296-020-50v3

72296-020-15v3